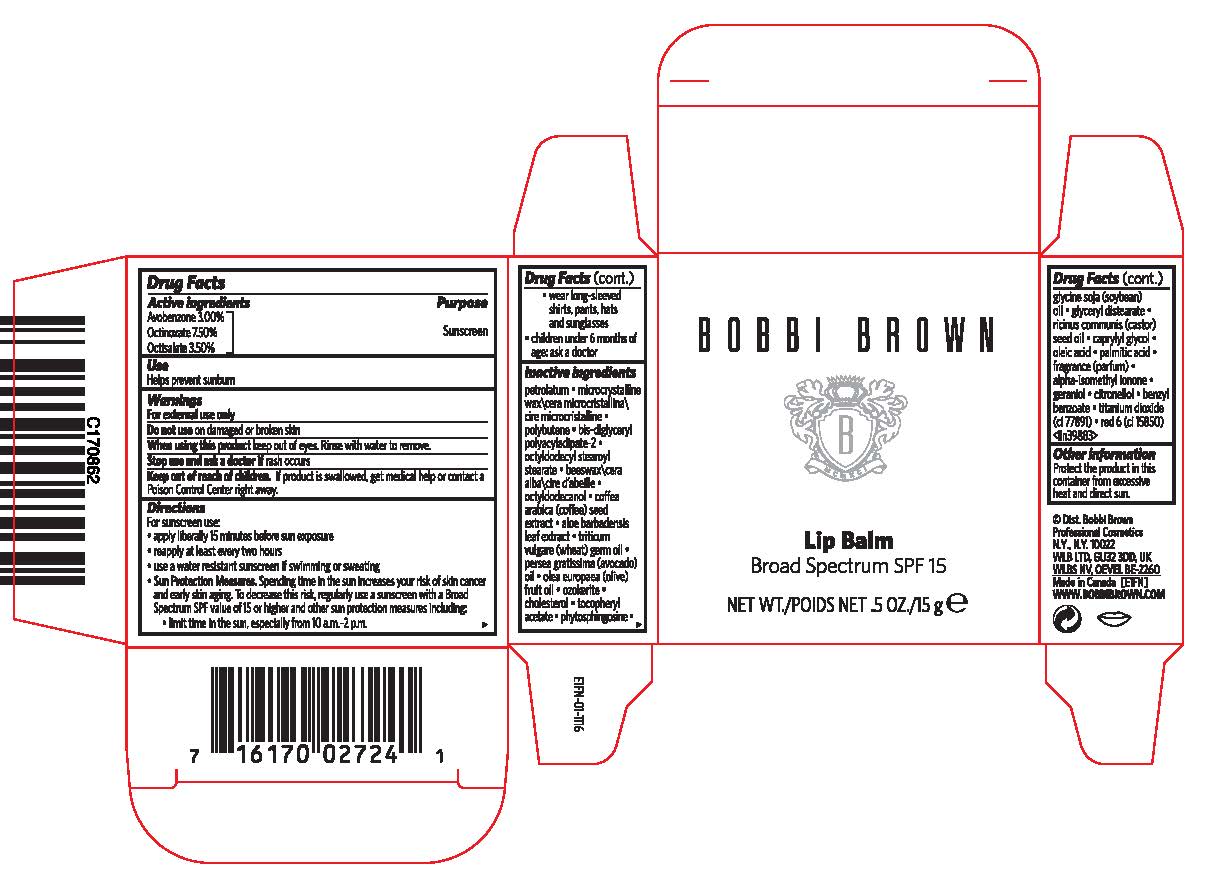 DRUG LABEL: BOBBI BROWN LIP BALM BROAD SPECTRUM SPF 15
NDC: 64141-019 | Form: LIPSTICK
Manufacturer: Bobbi Brown Professional Cosmetics Inc.
Category: otc | Type: HUMAN OTC DRUG LABEL
Date: 20241216

ACTIVE INGREDIENTS: AVOBENZONE 3 g/100 g; OCTINOXATE 7.5 g/100 g; OCTISALATE 3.5 g/100 g
INACTIVE INGREDIENTS: PETROLATUM; MICROCRYSTALLINE WAX; OCTYLDODECYL STEAROYL STEARATE; YELLOW WAX; OCTYLDODECANOL; ARABICA COFFEE BEAN; ALOE VERA LEAF; WHEAT GERM OIL; AVOCADO OIL; OLIVE OIL; CHOLESTEROL; .ALPHA.-TOCOPHEROL ACETATE; PHYTOSPHINGOSINE; SOYBEAN OIL; GLYCERYL DISTEARATE; CASTOR OIL; CAPRYLYL GLYCOL; OLEIC ACID; PALMITIC ACID; ISOMETHYL-.ALPHA.-IONONE; GERANIOL; .BETA.-CITRONELLOL, (R)-; BENZYL BENZOATE; TITANIUM DIOXIDE; D&C RED NO. 6

BOBBI BROWN LIP BALM BROAD SPECTRUM SPF 15

Drug Facts

Active Ingredients

Avobenzone 3.00%
Octinoxate 7.50%
Octisalate 3.50%

Purpose

Sunscreen

Use

Helps prevent sunburn

Warnings

For external use only

Do not use on damaged or broken skin

When using this product keep out of eyes. Rinse with water to remove.

Stop use and ask a doctor if rash occurs

Keep out of reach of children. If product is swallowed, get medical help or contact a Poison Control Center right away.

Directions

For sunscreen use:

- apply liberally 15 minutes before sun exposure
- reapply at least every two hours
- use a water resistant sunscreen if swimming or sweating
- Sun Protection Measures. Spending time in the sun increases your risk of skin cancer and early skin aging. To decrease this risk, regularly use a sunscreen with a Broad Spectrum SPF value of 15 or higher and other sun protection measures including:
  - limit time in the sun, especially from 10 a.m.–2 p.m.
  - wear long-sleeved shirts, pants, hats and sunglasses
- children under 6 months of age: ask a doctor

Inactive ingredients

petrolatum ■ microcrystalline wax\cera microcristallina\cire microcristalline ■ polybutene ■ bis-diglyceryl polyacyladipate-2 ■ octyldodecyl stearoyl stearate ■ beeswax\cera alba\cire d abeille ■ octyldodecanol ■ coffea arabica (coffee) seed extract ■ aloe barbadensis leaf extract ■ triticum vulgare (wheat) germ oil ■ persea gratissima (avocado) oil ■ olea europaea (olive) fruit oil ■ ozokerite ■ cholesterol ■ tocopheryl acetate ■ phytosphingosine ■ glycine soja (soybean) oil ■ glyceryl distearate ■ ricinus communis (castor) seed oil ■ caprylyl glycol ■ oleic acid ■ palmitic acid ■ fragrance (parfum) ■ alpha-isomethyl ionone ■ geraniol ■ citronellol ■ benzyl benzoate ■ titanium dioxide (ci 77891) ■ red 6 (ci 15850) <iln39883>

Other information

Protect the product in this container from excessive heat and direct sun.

PRINCIPAL DISPLAY PANEL - 15 g Jar Carton

BOBBI BROWN

Lip Balm
Broad Spectrum SPF 15

NET WT. .5 OZ./15 g e